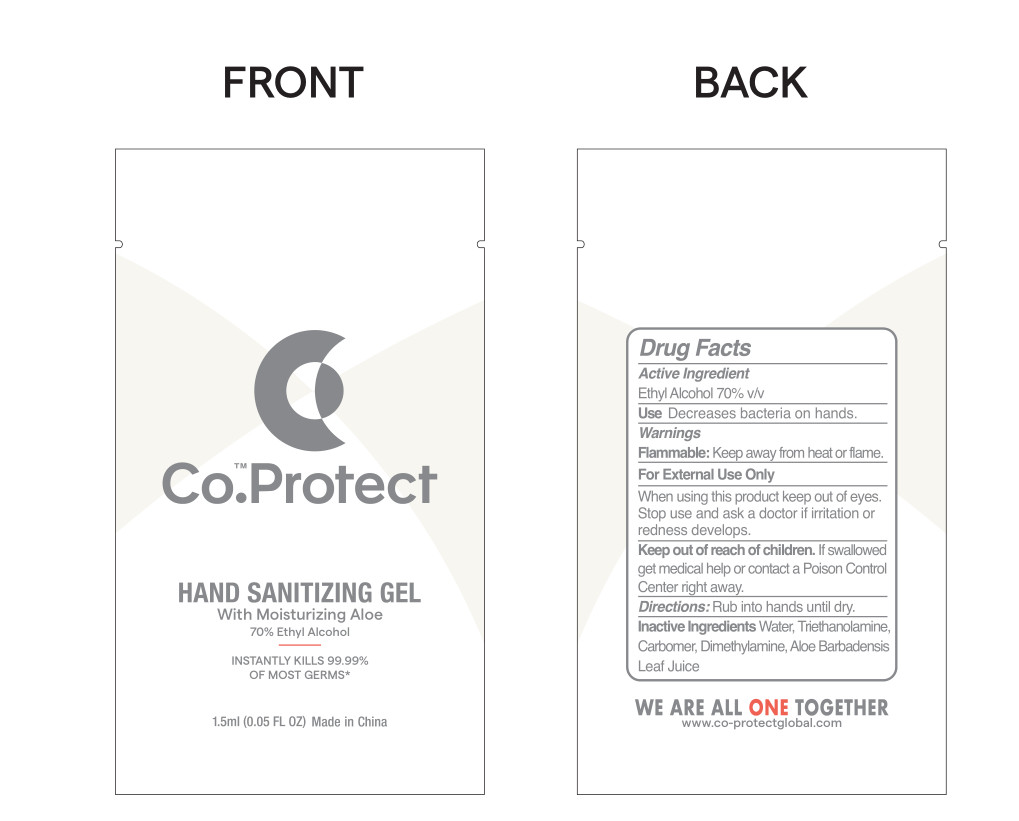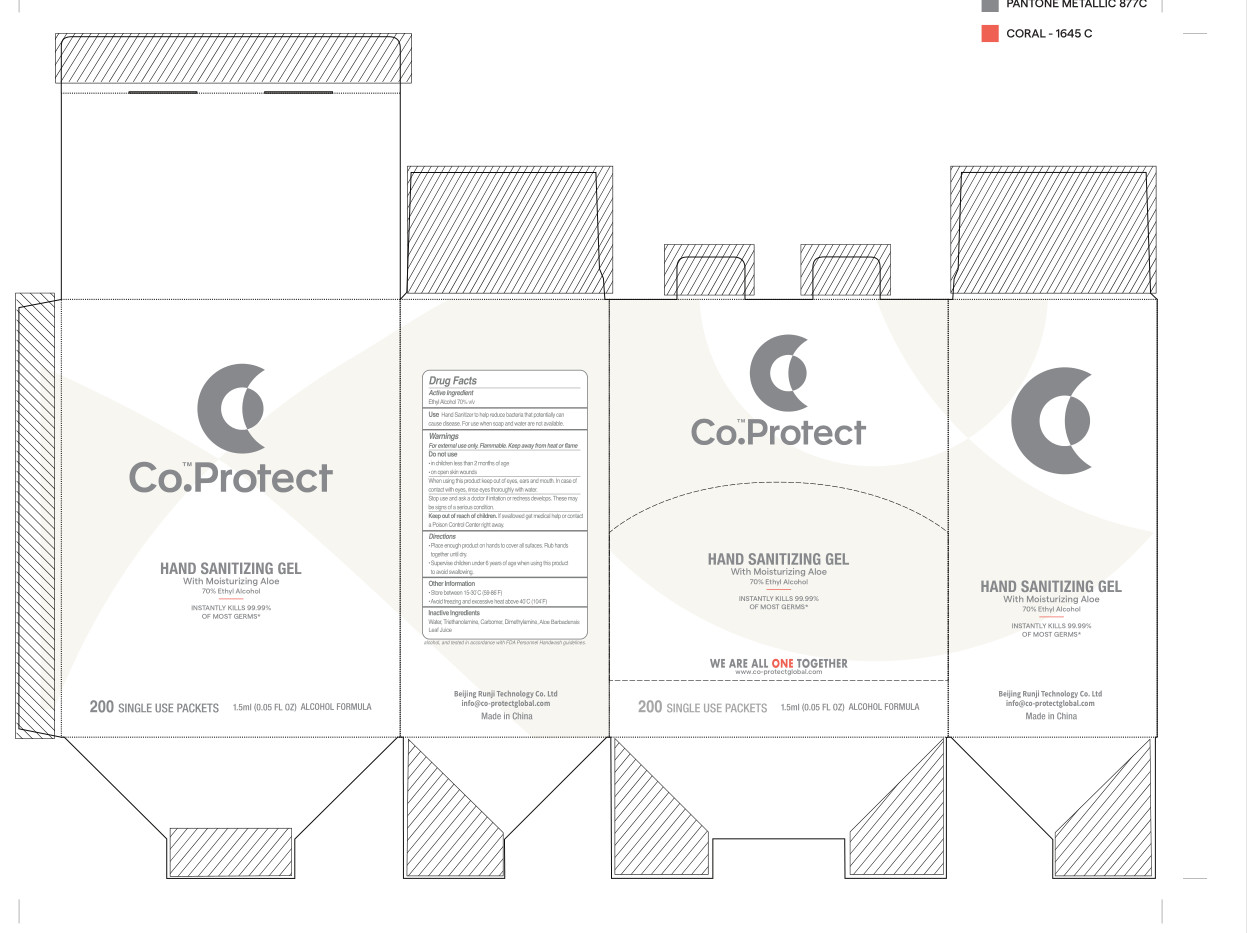 DRUG LABEL: CO-PROTECT HAND SANITIZERGEL
NDC: 41500-010 | Form: GEL
Manufacturer: Beijing Runyi Technology Co., Ltd
Category: otc | Type: HUMAN OTC DRUG LABEL
Date: 20200824

ACTIVE INGREDIENTS: ALCOHOL 1.05 mL/1.5 mL
INACTIVE INGREDIENTS: ALOE VERA LEAF; WATER; CARBOMER HOMOPOLYMER, UNSPECIFIED TYPE; DIMETHYLAMINE; TROLAMINE

DOSAGE AND ADMINISTRATION

1.Store between 15-30°C(59-86°F).
2.Avoid freezing and excessive heat above 40°C(104°F).

INACTIVE INGREDIENT

Water, Carbomer, Triethanolamine, Dimethylamine, Aloe Barbadensis Leaf Juice

INDICATIONS AND USAGE

Place enough product on hands to cover all sufaces.Rub hands together until dry.

ACTIVE INGREDIENT

Ethyl Alcohol

Keep out of reach of children. lf swallowed get medical help or contact a Poison Control Center right away.

PURPOSE

Disinfection
Sterilization
No Rinseing

WARNINGS

For external use only. Flammable.Keep away from heat or flame